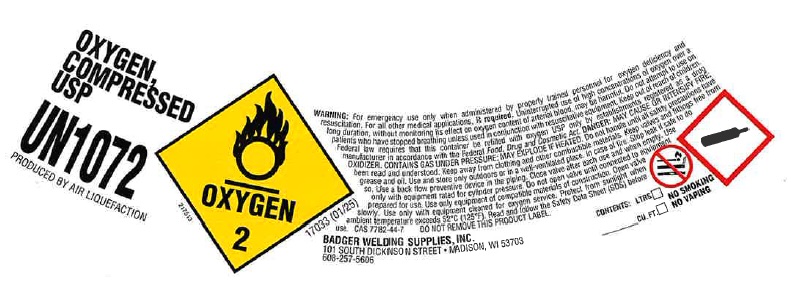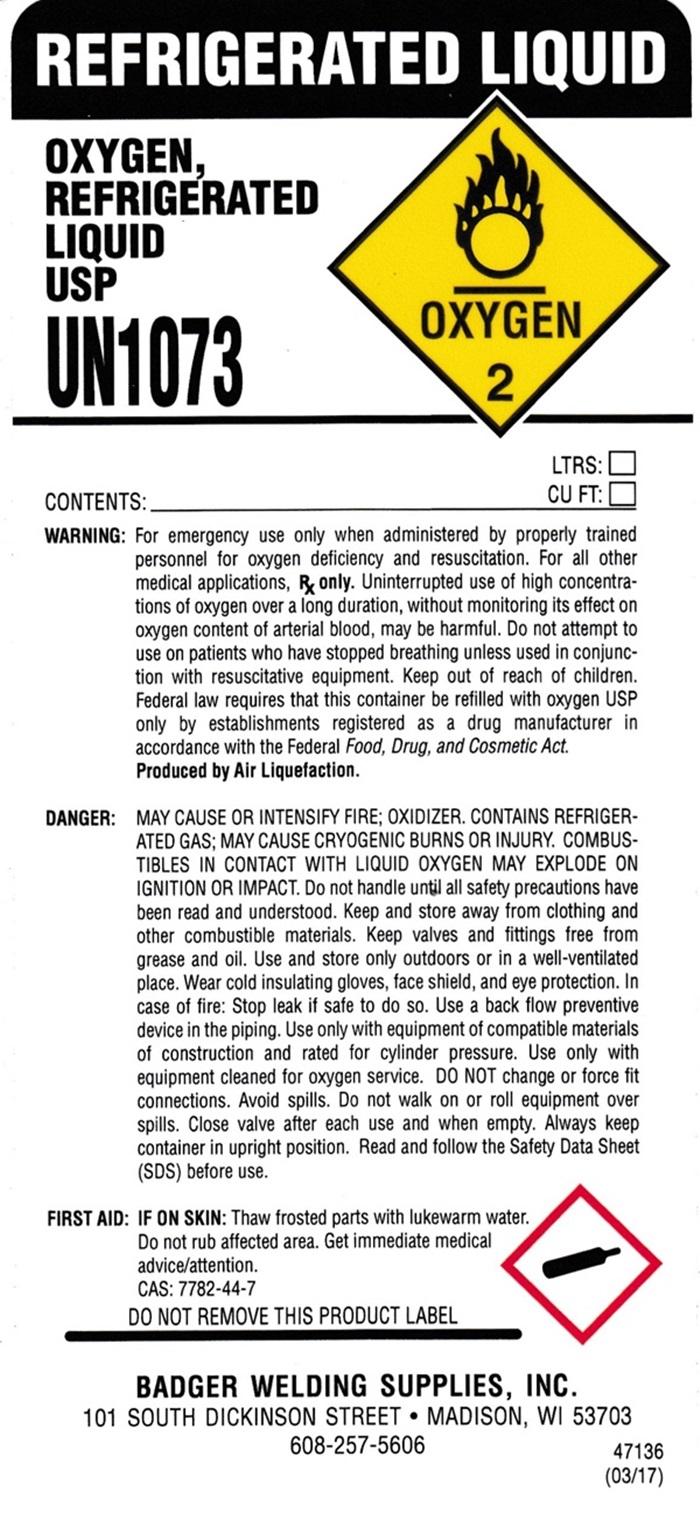 DRUG LABEL: OXYGEN
NDC: 12121-001 | Form: GAS
Manufacturer: Badger Welding Supplies, Inc.
Category: prescription | Type: HUMAN PRESCRIPTION DRUG LABEL
Date: 20250707

ACTIVE INGREDIENTS: OXYGEN 99 L/100 L

OXYGEN - 001

OXYGEN COMPRESSED USP LABEL

OXYGEN COMPRESSED USP

UN 1072

PRODUCED BY AIR LIQUEFACTION

OXYGEN 2

17033 (01/25)

WARNING: For emergency use only when administered by properly trained personnel for oxygen deficiency and resuscitation. For all other medical applications, Rx required. Uninterrupted use of high concentrations of oxgen over a long duration, without monitoring its effect on oxygen content of arterial blood, may be harmful. Do not attempt to use on patients who have stopped breathing unless used in conjunction with resuscitative equipment. Keep out of reach of children. Federal law requires that this container be refilled with oxygen USP only by establishments registered as a drug manufacturer in accordance with the Federal Food, Drug and Cosmetic Act. DANGER: MAY CAUSE OR INTENSIFY FIRE; OXIDIZER. CONTAINS GAS UNDER PRESSURE. MAY EXPLODE IF HEATED. Do not handle until all safety precautions have been read and understood. Keep and store away from clothing and other combustible materials. Keep valves and fittings free from grease and oil. Use and store only outdoors or in a well-ventilated place. In case of fire:Stop leak if safe to do so. Use a back flow preventive device in the piping. Close valve after each use and when empty. Use only with equipment rated for cylinder pressure. Do not open valve until connected to equipment prepared for use. Use only equipment of compatible materials of constructions. Open valve slowly. Use only with equipment cleaned for oxygen service. Protect from sunlight when ambient temperature exceeds 52°C (125°F). Read and follow the Safety Data Sheet (SDS) before use. CAS: 7782-44-7 DO NOT REMOVE THIS PRODUCT LABEL

BADGER WELDING SUPPLIES, INC.
101 SOUTH DICKSON STREET MADISON WI 53703

608-257-5606

CONTENTS: LTRS. __________ CU. FT. _______________

NO SMOKING

NO VAPING

OXYGEN REFRIGERATED LIQUID USP LABEL

REFIGERATED LIQUID

OXYGEN REFRIGERATED LIQUID USP

UN 1073

OXYGEN 2

CONTENTS: _____________________________________LTRS: ______________ CU. FT: _______________________

WARNING: For emergency use only when administered by properly trained personnel for oxygen deficiency and resuscitation. For all other medical applications, Rx Only. Uninterrupted use of high concentrations of oxgen over a long duration, without monitoring its effect on oxygen content of arterial blood, may be harmful. Do not attempt to use on patients who have stopped breathing unless it is in conjunction with resuscitative equipment. Keep out of reach of children. Federal law requires that this container be refilled with oxygen USP only by establishments registered as a drug manufacture in accordance with the Federal Food, Drug and Cosmetic Act.

Produced by Air Liquefaction.

DANGER: MAY CAUSE OR INTENSIFY FIRE; OXIDIZER. CONTAINS REFIGERATED GAS: MAY CAUSE CRYOGENIC BURNS OR INJURY. COMBUSTIBLES IN CONTACT WITH LIQUID OXYGEN MAY EXPLODE ON IGNITION OR IMPACT. Do not handle until all safety precautions have been read and understood. Keep and store away from clothing and other combustible materials. Keep valves and fittings free from grease and oil. Use and store only outdoors or in a well-ventilated place. Wear cold insulating gloves, face shield, and eye protection. In case of fire:Stop leak if safe to do so. Use a back flow preventive device in the piping. Use only with equipment of compatible materials of construction and rated for cylinder pressure. Use only with equipment cleaned for oxygen service. DO NOT change or force fit connections. Avoid spills. Do not walk or roll equipment over spills. Close valve after each use and when empty. Always keep container in upright position. Read and follow the Safety Data Sheet (SDS) before use.

FIRST AID: IF ON SKIN: Thaw frosted parts with lukewarm water. Do not rub affected area. Get immediate medical advise/attention.

CAS: 7782-44-7

DO NOT REMOVE THIS PRODUCT LABEL

BADGER WELDING SUPPLIES, INC.
101 SOUTH DICKSON STREET • MADISON, WI 53703

608-257-5606

47136 (03/17)